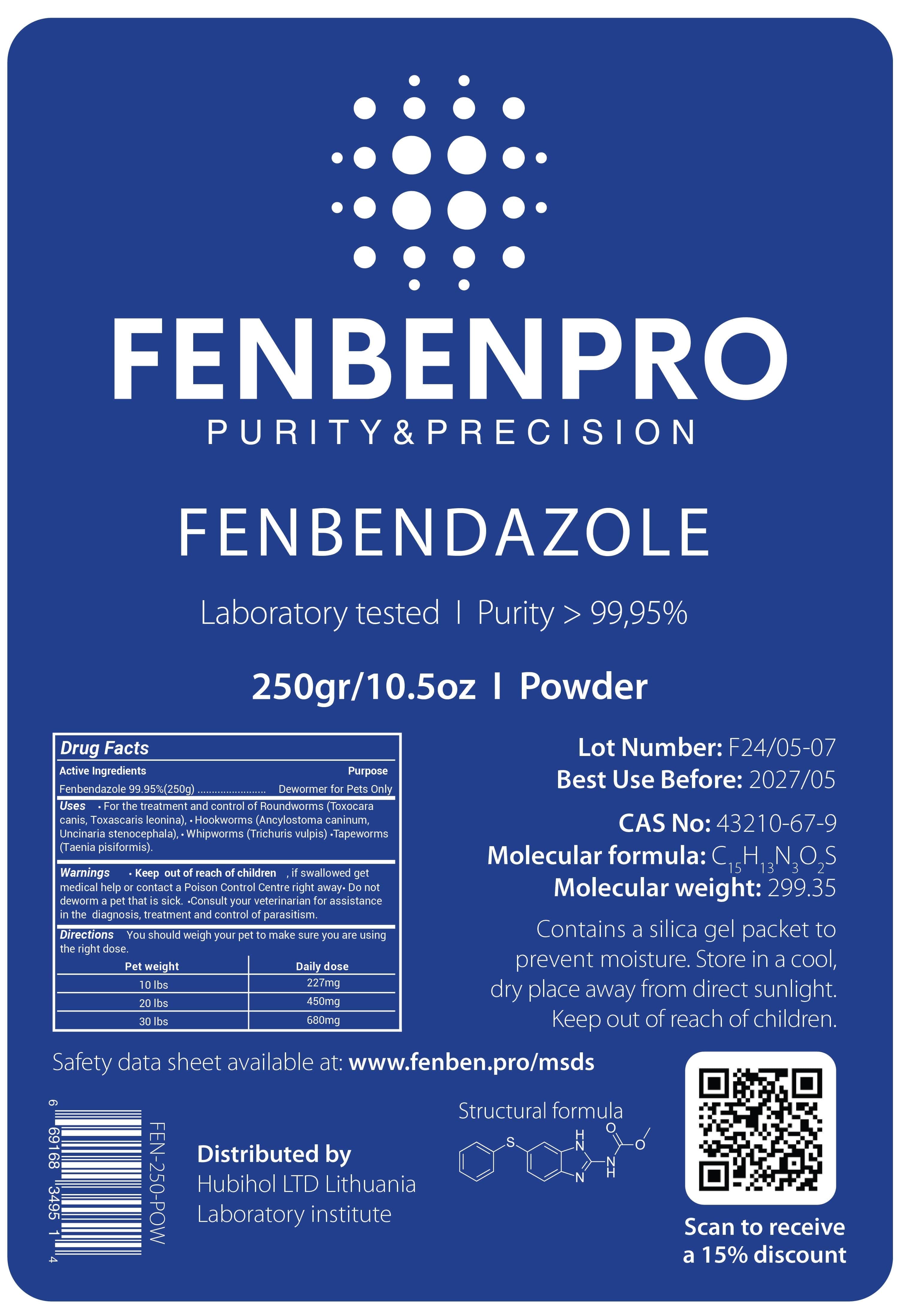 DRUG LABEL: FENBENPRO PURITY and PRECISION FENBENDAZOLE
NDC: 86217-0009 | Form: POWDER
Manufacturer: HUBIHOL, UAB
Category: other | Type: BULK INGREDIENT - ANIMAL DRUG
Date: 20250211

ACTIVE INGREDIENTS: FENBENDAZOLE 250 g/250 g

FENBENPRO PURITY and PRECISION FENBENDAZOLE

Active Ingredients

Fenbendazole 99.95% (500g)

Package Labeling

6
FENBENPRO
Drug Facts
Active Ingredients
PURITY & PRECISION
FENBENDAZOLE
Laboratory tested | Purity > 99,95%
250gr/10.5oz I Powder
Purpose
Fenbendazole 99.95%(250g).................... Dewormer for Pets Only Uses ⚫ For the treatment and control of Roundworms (Toxocara canis, Toxascaris leonina),⚫ Hookworms (Ancylostoma caninum, Uncinaria stenocephala), Whipworms (Trichuris vulpis) ⚫Tapeworms (Taenia pisiformis).
Warnings
•
• Keep out of reach of children, if swallowed get medical help or contact a Poison Control Centre right away. Do not deworm a pet that is sick. Consult your veterinarian for assistance in the diagnosis, treatment and control of parasitism. Directions You should weigh your pet to make sure you are using the right dose.
Pet weight
10 lbs
20 lbs
30 lbs
Daily dose
227mg
450mg
680mg
Lot Number: F24/05-07 Best Use Before: 2027/05
CAS No: 43210-67-9
Molecular formula: C1H12N2O,S
15 13
3
2
Molecular weight: 299.35
Contains a silica gel packet to prevent moisture. Store in a cool, dry place away from direct sunlight. Keep out of reach of children.
Safety data sheet available at: www.fenben.pro/msds
Structural formula
69168
3495 1
4
FEN-250-POW
Distributed by
Hubihol LTD Lithuania Laboratory institute
S.
N
N
N
Scan to receive
a 15% discount